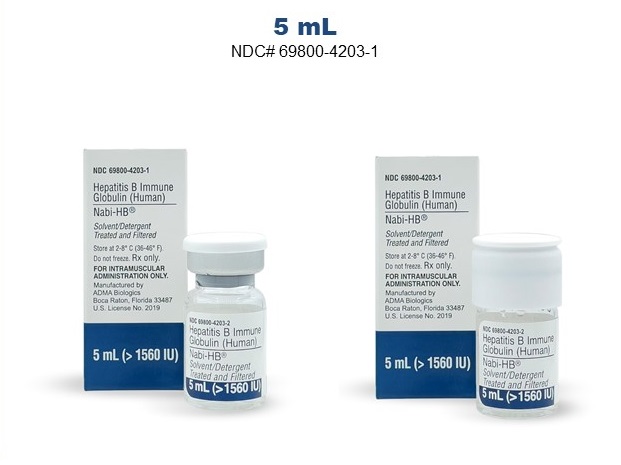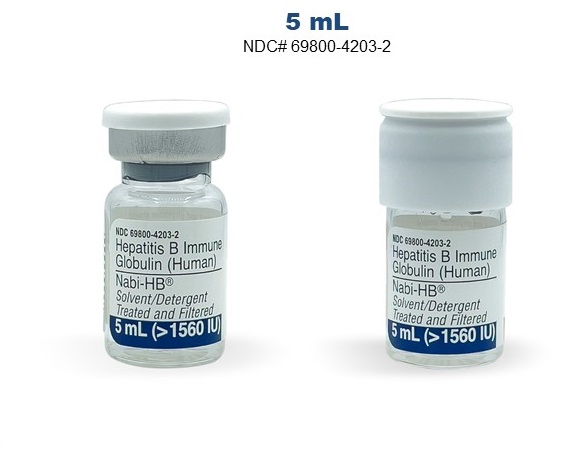 DRUG LABEL: Nabi-HB
NDC: 69800-4203 | Form: LIQUID
Manufacturer: ADMA Biologics, Inc.
Category: prescription | Type: HUMAN PRESCRIPTION DRUG LABEL
Date: 20250410

ACTIVE INGREDIENTS: HUMAN HEPATITIS B VIRUS IMMUNE GLOBULIN 1560 [iU]/5 mL
INACTIVE INGREDIENTS: GLYCINE; SODIUM CHLORIDE; POLYSORBATE 80

Hepatitis B Immune Globulin (Human)
Nabi-HB®
Solvent/Detergent Treated and Filtered

DESCRIPTION

Hepatitis B Immune Globulin (Human), Nabi-HB, is a sterile solution of immunoglobulin (5 ± 1% protein) containing antibodies to hepatitis B surface antigen (anti-HBs). It is prepared from plasma donated by individuals with high titers of anti-HBs. The plasma is processed using a modified Cohn 6 / Oncley 9 cold-alcohol fractionation process^1,2 with two added viral reduction steps described below. Nabi-HB is formulated in 0.042-0.108 M sodium chloride, 0.10-0.20 M glycine, and 0.005-0.050% polysorbate 80, at pH 5.8-6.5. The product is supplied as a nonturbid sterile liquid in single dose vials and appears as clear to opalescent. It contains no preservative and is intended for single use by the intramuscular route only.

Each plasma donation used for the manufacture of Nabi-HB is tested for the presence of hepatitis B virus (HBV) surface antigen (HBsAg), human immunodeficiency viruses (HIV) 1/2, and hepatitis C virus (HCV) antibodies. In addition, pooled samples of source plasma used in the manufacture of this product are tested by FDA licensed Nucleic Acid Testing (NAT) for HIV and HCV and found to be negative. Investigational NAT for hepatitis A virus (HAV) and HBV is also performed on pooled samples of all source plasma used, and found to be negative; however, the significance of a negative result has not been established. Investigational NAT for parvovirus B19 (B19) is also performed on pooled samples of all source plasma and the limit for B19 DNA in a manufacturing pool is set not to exceed 10^4 IU/mL.

The manufacturing steps for Nabi-HB are designed to reduce the risk of transmission of viral disease. The solvent/detergent treatment step, using tri- n-butyl phosphate and Triton® X-100, is effective in inactivating known enveloped viruses such as hepatitis B virus (HBV), hepatitis C virus (HCV), and human immunodeficiency virus (HIV)^3. Virus filtration, using a Planova® 35 nm Virus Filter, is effective in reducing some known enveloped and non-enveloped viruses^4. The inactivation and reduction of known enveloped and non-enveloped model viruses were validated in laboratory studies as summarized in the following table:

Table 1 Log Reduction of Test Viruses^5
 | Test Virus
 | HIV | BVD | PRV | EMC | PPV
Model Virus: | HIV | HCV | HBV | Hepatitis A | PVB19
Envelope/Genome: | yes/RNA | yes/RNA | yes/DNA | no/RNA | no/DNA
Manufacturing Step
Precipitation of Cohn; Fraction III | >5.9 | 3.6 | 3.7 | 4.4 | 3.9
Cuno Filtration | NT | NT | NT | >6.6 | 5.4
Solvent/Detergent | >4.2 | >6.9 | >6.4 | NT | NT
Nanofiltration | >7.4 | >6.9 | >5.7 | 3.0 | 0.7*
Cumulative | >17.5 | >17.4 | >15.8 | >14.0 | 9.3
BVD = Bovine Viral Diarrhea Virus EMC = Encephalomyocarditis Virus HIV = Human Immunodeficiency Virus |  | PVB19 = Parvovirus B19 PPV = Porcine Parvovirus PRV = Pseudorabies Virus |  | NT = not tested * Value not included in cumulative clearance

Product potency is expressed in international units (IU) by comparison to the World Health Organization (WHO) standard. Each milliliter (mL) of product contains greater than 312 IU anti-HBs. The potency of each milliliter of Nabi-HB exceeds the potency of anti-HBs in a U.S. reference hepatitis B immune globulin (FDA). The U.S. reference has been tested by Biotest Pharmaceuticals against the WHO standard and found to be equal to 208 IU/mL.

CLINICAL PHARMACOLOGY

Hepatitis B Immune Globulin (Human) products provide passive immunization for individuals exposed to the hepatitis B virus as evidenced by a reduction in the attack rate of hepatitis B following use^6-9.

Clinical studies^10,11 conducted prior to 1983 with hepatitis B immune globulins similar to Nabi-HB indicate the advantage of simultaneous administration of hepatitis B vaccine and Hepatitis B Immune Globulin (Human). The Centers for Disease Control and Prevention Advisory Committee on Immunization Practices (ACIP) advises that the combination prophylaxis be provided in certain instances of exposure based upon the increased efficacy found with that regimen in neonates^12 . Cases of hepatitis B are rarely seen following exposure to HBV in persons with preexisting anti-HBs. However, no prospective studies have been performed on the efficacy of concurrent hepatitis B vaccine and Hepatitis B Immune Globulin (Human) administration following parenteral exposure, mucous membrane contact, or oral ingestion in adults.

Infants born to HBsAg-positive mothers are at risk of being infected with HBV and becoming chronic carriers^13. The risk is especially great if the mother is also HBeAg-positive^14. Studies conducted with hepatitis B immune globulins similar to Nabi-HB indicated that for an infant with perinatal exposure to an HBsAg-positive and HBeAg-positive mother, a regimen combining one dose of Hepatitis B Immune Globulin (Human) at birth with the hepatitis B vaccine series started soon after birth is 85-98% effective in preventing development of the HBV carrier state^15-17. Regimens involving either multiple doses of Hepatitis B Immune Globulin (Human) alone or the vaccine series alone have a 70-90% efficacy, while a single dose of Hepatitis B Immune Globulin (Human) alone has 50% efficacy^18.

Since infants have close contact with primary caregivers and they have a higher risk of becoming HBV carriers after acute HBV infection, prophylaxis of an infant less than 12 months of age with Hepatitis B Immune Globulin (Human) and hepatitis B vaccine is indicated if the mother or primary caregiver has acute HBV infection^19 .

Sexual partners of HBsAg-positive persons are at increased risk of acquiring HBV infection. A single dose of Hepatitis B Immune Globulin (Human) is 75% effective if administered within two weeks of the last sexual exposure to a person with acute hepatitis B^19.

Pharmacokinetics

Pharmacokinetics trials^20 of Nabi-HB, Hepatitis B Immune Globulin (Human), given intramuscularly to 50 healthy volunteers demonstrated pharmacokinetic parameters similar to those reported by Scheiermann and Kuwert^21 . The half-life for Nabi-HB was 23.1 ± 5.5 days. The clearance rate was 0.35 ± 0.12 L/day and the volume of distribution was 11.2 ± 3.4 L.

Maximum concentration of Nabi-HB was reached in 6.5 ± 4.3 days. The maximum concentration of anti-HBs and the area under the time-concentration curve achieved by Nabi-HB were bioequivalent to that of another licensed Hepatitis B Immune Globulin (Human) when compared in the same pharmacokinetics trial. Comparability of pharmacokinetics between Nabi-HB and a commercially available hepatitis B immunoglobulin indicate that similar efficacy of Nabi-HB should be inferred.

INDICATIONS AND USAGE

Nabi-HB, Hepatitis B Immune Globulin (Human), is indicated for treatment of acute exposure to blood containing HBsAg, perinatal exposure of infants born to HBsAg-positive mothers, sexual exposure to HBsAg-positive persons and household exposure to persons with acute HBV infec- tion in the following settings:

- Acute Exposure to Blood Containing HBsAg:

Following either parenteral exposure (needlestick, bite, sharps), direct mucous membrane contact (accidental splash), or oral ingestion (pipetting accident), involving HBsAg-positive materials such as blood, plasma, or serum.

- Perinatal Exposure of Infants Born to HBsAg-positive Mothers:

Infants born to mothers positive for HBsAg with or without HBeAg^12.

- Sexual Exposure to HBsAg-positive Persons:

Sexual partners of HBsAg-positive persons.

- Household Exposure to Persons with Acute HBV Infection:

Infants less than 12 months old whose mother or primary caregiver is positive for HBsAg. Other household contacts with an identifiable blood exposure to the index patient.

Nabi-HB is indicated for intramuscular use only.

CONTRAINDICATIONS

Individuals known to have had an anaphylactic or severe systemic reaction to human globulin should not receive Nabi-HB, Hepatitis B Immune Globulin (Human), or any other human immune globulin. Nabi-HB contains not more than 40 micrograms per mL IgA. Individuals who are deficient in IgA have the potential to develop antibodies against IgA and anaphylactic reactions. The physician must weigh the potential benefit of treatment with Nabi-HB against the potential for hypersensitivity reactions.

WARNINGS

In patients who have severe thrombocytopenia or any coagulation disorder that would contraindicate intramuscular injections, Nabi-HB, Hepatitis B Immune Globulin (Human), should be given only if the expected benefits outweigh the potential risks.

Nabi-HB is made from human plasma. Products made from human plasma may contain infectious agents, e.g., viruses, and theoretically, the Creutzfeldt-Jakob disease (CJD) agent. The risk that such products can transmit an infectious agent has been reduced by screening plasma donors for prior exposure to certain viruses, by testing for the presence of certain current viral infections, and by inactivating and/or reducing certain viruses. The Nabi-HB manufacturing process includes a solvent/detergent treatment step (using tri- n-butyl phosphate and Triton® X-100) that is effective in inactivating known enveloped viruses such as HBV, HCV, and HIV. Nabi-HB is filtered using a Planova® 35 nm Virus Filter that is effective in reducing the levels of some enveloped and non-enveloped viruses. These two processes are designed to increase product safety. Despite these measures, such products can still potentially transmit disease. There is also the possibility that unknown infectious agents may be present in such products. ALL infections thought by a physician possibly to have been transmitted by this product should be reported by the physician or other health care provider to ADMA Biologics at 1-800-458-4244. The physician should discuss the risks and benefits of this product with the patient.

PRECAUTIONS

General

Nabi-HB, Hepatitis B Immune Globulin (Human), must be administered only intramuscularly for post-exposure prophylaxis. The preferred sites for intramuscular injections are the anterolateral aspect of the upper thigh and the deltoid muscle. If the buttock is used due to the volume to be injected, the central region should be avoided; only the upper, outer quadrant should be used, and the needle should be directed anterior (i.e., not inferior or perpendicular to the skin) to minimize the possibility of involvement with the sciatic nerve^22 .

The 50 healthy volunteers who received Nabi-HB in pharmacokinetic studies were followed for 84 days for possible development of anti-HCV antibodies. No subject seroconverted.

Drug Interactions

Vaccination with live virus vaccines should be deferred until approximately three months after administration of Nabi-HB, Hepatitis B Immune Globulin (Human). It may be necessary to revaccinate persons who received Nabi-HB shortly after live virus vaccination.
There are no available data on concomitant use of Nabi-HB and other drugs; therefore, Nabi-HB should not be mixed with other drugs.

Pregnancy Category C

Animal reproduction studies have not been conducted with Nabi-HB. It is also not known whether Nabi-HB can cause fetal harm when administered to a pregnant woman or can affect a woman’s ability to conceive. Nabi-HB should be given to a pregnant woman only if clearly indicated.

Nursing Mothers

It is not known whether this drug is excreted in human milk. Because many drugs are excreted in human milk, caution should be exercised when Nabi-HB is administered to a nursing mother.

Pediatric Use

Safety and effectiveness in the pediatric population have not been established for Nabi-HB. However, the safety and effectiveness of similar hepatitis B immune globulins have been demonstrated in infants and children^12.

Geriatric Use

Clinical studies of Nabi-HB did not include sufficient numbers of subjects aged 65 and over to determine whether they respond differently than younger subjects. Other reported clinical experience has not identified differences in responses between the elderly and younger patients.

ADVERSE REACTIONS SECTION

Fifty male and female volunteers received Nabi-HB, Hepatitis B Immune Globulin (Human), intramuscularly in pharmacokinetics trials^20. The number of patients with reactions related to the administration of Nabi-HB included local reactions such as erythema 6 (12%) and ache 2 (4%) at the injection site, as well as systemic reactions such as headache 7 (14%), myalgia 5 (10%), malaise 3 (6%), nausea 2 (4%), and vomiting 1 (2%). The majority (92%) of reactions were reported as mild. The following adverse events were reported in the pharmacokinetics trials and were considered probably related to Nabi-HB: elevated alkaline phosphatase 2 (4%), ecchymosis 1 (2%), joint stiffness 1 (2%), elevated AST 1 (2%), decreased WBC 1 (2%), and elevated creatinine 1 (2%). All adverse events were mild in intensity. There were no serious adverse events.

No anaphylactic reactions with Nabi-HB have been reported. However, these reactions, although rare, have been reported following the injection of human immune globulins^23.

OVERDOSAGE

Although no data are available, clinical experience reported with other human immune globulins suggests that the only manifestations of overdose with Nabi-HB, Hepatitis B Immune Globulin (Human), would be pain and tenderness at the injection site.

DOSAGE AND ADMINISTRATION

This product is for intramuscular use only. The use of this product by the intravenous route is not indicated. Parenteral drug products should be inspected visually for particulate matter and discoloration prior to administration.

It is important to use a separate vial, sterile syringe, and needle for each individual patient, in order to prevent transmission of infectious agents from one person to another. Any vial of Nabi-HB, Hepatitis B Immune Globulin (Human) that has been entered should be used promptly. Do not reuse or save for future use. This product contains no preservative; therefore, partially used vials should be discarded immediately.

Hepatitis B Immune Globulin (Human) may be administered at the same time (but at a different site), or up to one month preceding hepatitis B vaccination without impairing the active immune response to hepatitis B vaccine^11.

- Acute Exposure to Blood Containing HBsAg

Table 2 summarizes prophylaxis for percutaneous (needlestick, bite, sharps), ocular, or mucous membrane exposure to blood according to the source of exposure and vaccination status of the exposed person. For greatest effectiveness, passive prophylaxis with Hepatitis B Immune Globulin (Human) should be given as soon as possible after exposure, as its value after seven days following exposure is unclear^12. An injection of 0.06 mL/kg of body weight should be administered intramuscularly as soon as possible after exposure and within 24 hours, if possible. Consult the hepatitis B vaccine package insert for dosage information regarding the vaccine.

For persons who refuse hepatitis B vaccine or are known non-responders to vaccine, a second dose of Hepatitis B Immune Globulin (Human) should be given one month after the first dose^12.

Table 2 Recommendations for Hepatitis B Prophylaxis Following Percutaneous or Permucosal Exposure^12
 | Exposed Person
Source | Unvaccinated | Vaccinated
HBsAg-positive | 1. Hepatitis B Immune Globulin (Human) X1 immediately* 2. Initiate HB vaccine series† | 1. Test exposed person for anti-HBs 2. If inadequate antibody‡ , Hepatitis B Immune Globulin (Human) X 1 immediately plus either HB vaccine booster dose or second dose of Hepatitis B Immune Globulin (Human) one month later§
Known Source - High Risk for HBsAg-positive | 1. Initiate HB vaccine series 2. Test source for HBsAg. If positive, Hepatitis B Immune Globulin (Human) X 1 | 1. Test source for HBsAg only if exposed is vaccine nonresponder; if source is HBsAg-positive, give Hepatitis B Immune Globulin (Human) X 1 immediately plus either HB vaccine booster dose or second dose of Hepatitis B Immune Globulin (Human) one month later§.
Known Source - Low Risk for HBsAg-positive | Initiate HB vaccine series | Nothing required
Unknown Source | Initiate HB vaccine series | Nothing required
* Hepatitis B Immune Globulin (Human) dose of 0.06 mL/kg IM.
† See manufacturer’s recommendation for appropriate dose.
‡ Less than 10 mIU/mL anti-HBs by radioimmunoassay, negative by enzyme immunoassay.
§ Two doses of Hepatitis B Immune Globulin (Human) is preferred if no response after at least four doses of vaccine.

- Prophylaxis of Infants Born to Mothers who are Positive for HBsAg with or without HBeAg

Table 3 contains the recommended schedule of hepatitis B prophylaxis for infants born to mothers that are either known to be positive for HBsAg or have not been screened. Infants born to mothers known to be HBsAg-positive should receive 0.5 mL Hepatitis B Immune Globulin (Human) after physiologic stabilization of the infant and preferably within 12 hours of birth. The hepatitis B vaccine series should be initiated simultaneously, if not contraindicated, with the first dose of the vaccine given concurrently with the Hepatitis B Immune Globulin (Human), but at a different site. Subsequent doses of the vaccine should be administered in accordance with the recommendations of the manufacturer.

Women admitted for delivery, who were not screened for HBsAg during the prenatal period, should be tested. While test results are pending, the newborn infant should receive hepatitis B vaccine within 12 hours of birth (see manufacturers’ recommendations for dose). If the mother is later found to be HBsAg-positive, the infant should receive 0.5 mL Hepatitis B Immune Globulin (Human) as soon as possible and within seven days of birth; however, the efficacy of Hepatitis B Immune Globulin (Human) administered after 48 hours of age is not known^10,19. Testing for HBsAg and anti-HBs is recommended at 12-15 months of age. If HBsAg is not detectable and anti-HBs is present, the child has been protected^12.

Table 3 Recommended Schedule of Hepatitis B Immunoprophylaxis to Prevent Perinatal Transmission of Hepatitis B Virus Infection^19
 | Age of Infant
Administer | Infant Born to mother known to be HBsAg-positive | Infant born to mother not screened for HBsAg
First Vaccination* | Birth (within 12 hours) | Birth (within 12 hours)
Hepatitis B Immune Globulin (Human)† | Birth (within 12 hours) | If mother is found to be HBsAg-positive, administer dose to infant as soon as possible, not later than 1 week after birth
Second Vaccination* | 1 month | 1-2 months
Third Vaccination* | 6 months‡ | 6 months‡
* See manufacturers’ recommendations for appropriate dose.
† 0.5 mL administered IM at a site different from that used for the vaccine.
‡ See ACIP recommendation.

- Sexual Exposure to HBsAg-positive Persons

All susceptible persons whose sexual partners have acute hepatitis B infection should receive a single dose of Hepatitis B Immune Globulin (Human) (0.06 mL/kg) and should begin the hepatitis B vaccine series, if not contraindicated, within 14 days of the last sexual contact or if sexual contact with the infected person will continue. Administering the vaccine with Hepatitis B Immune Globulin (Human) may improve the efficacy of post exposure treatment. The vaccine has the added advantage of conferring long-lasting protection^19.

- Household Exposure to Persons with Acute HBV Infection

Prophylaxis of an infant less than 12 months of age with 0.5 mL Hepatitis B Immune Globulin (Human) and hepatitis B vaccine is indicated if the mother or primary caregiver has acute HBV infection. Prophylaxis of other household contacts of persons with acute HBV infection is not indicated unless they had an identifiable blood exposure to the index patient, such as by sharing toothbrushes or razors. Such exposures should be treated
like sexual exposures. If the index patient becomes an HBV carrier, all household contacts should receive hepatitis B vaccine^19.

HOW SUPPLIED

Nabi-HB, Hepatitis B Immune Globulin (Human), is supplied as:

NDC Number | Contents
69800-4203-1 | a carton containing a 5 mL dose in a single-use vial (>1560 IU) and package insert

STORAGE

Refrigerate between 2 to 8 °C (36 to 46 °F). Do not freeze. Do not use after expiration date. Use within 6 hours after the vial has been entered.

REFERENCES

1. Cohn E.J., Strong W.L., Mulford D.J., Ashworth J.N., Melin M., Taylor H.L. Preparation and Properties of Serum and Plasma Proteins IV. A system for the separation into fractions of the protein and lipoprotein components of biological tissues and fluids. J Am Chem Soc 1946, 68: 459-475.
2. Oncley J.L, Melin M, Richert D.A, Cameron J. W, Gross P.M. The separation of antibodies, isoagglutinins, prothrombin, plasminogen and b1-lipoproteins into sub-fractions of human plasma. J Am Chem Soc 1949, 71:541-550.
3. Horowitz B: Investigations into the application of tri(n-butyl)phosphate/detergent mixtures to blood derivatives. Morgenthaler J (ed): Virus Inactivation in Plasma Products, Curr Stud Hematol Blood Transfus 1989; 56:83-96.
4. Burnouf T: Value of virus filtration as method for improving the safety of plasma products. Vox Sang 1996; 70:235-236.
5. Unpublished data on file, Viral Validation Study Reports, Biotest Pharmaceuticals.
6. Grady GF, and Lee VA: Hepatitis B immune globulin - prevention of hepatitis from accidental exposure among medical personnel. N Engl J Med 1975; 293:1067-1070.
7. Seeff LB, et al.: Type B hepatitis after needle-stick exposure: Prevention with hepatitis B immune globulin. Ann Int Med 1978; 88:285-293.
8. Krugman S, and Giles JP: Viral hepatitis, type B (MS-2-strain). Further observations on natural history and prevention. N Engl J Med 1973; 288:755-760.
9. Hoofnagle JH, et al.: Passive - active immunity from hepatitis B immune globulin. Ann Int Med 1979; 91:813-818.
10. Beasley RP, et al.: Efficacy of hepatitis B immune globulin for prevention of perinatal transmission of the hepatitis B virus carrier state: Final report of a randomized double-blind, placebo - controlled trial. Hepatology 1983; 3:135-141.
11. Szmuness W, et al.: Passive active immunisation against hepatitis B: Immunogenicity studies in adult Americans. Lancet 1981; 1:575-577.
12. Centers for Disease Control: Recommendations for protection against viral hepatitis. Recommendations of the Immunization Practices Advisory Committee (ACIP). MMWR 1985; 34(22):313-335.
13. Shiraki Y, et al.: Hepatitis B surface antigen and chronic hepatitis in infants born to asymptomatic carrier mothers. Am J Dis Child 1977; 131:644-647.
14. Beasley RP, et al.: The e antigen and vertical transmission of hepatitis B surface antigen. Am J Epidemiol 1977; 105:94-98.
15. Wong VCW, et al.: Prevention of the HBsAg carrier state in newborn infants of mothers who are chronic carriers of HBsAg and HBeAg by administration of hepatitis B vaccine and hepatitis B immunoglobulin: Double-blind randomized placebo-controlled study. Lancet 1984; 1:921-926.
16. Poovorawan Y, et al.: Long term hepatitis B vaccine in infants born to hepatitis B e antigen positive mothers. Archives of Diseases in Childhood 1997; 77:F47-F51.
17. Stevens CE, et al.: Perinatal Hepatitis B virus transmission in the United States: Prevention by passive-active immunization. JAMA 1985; 253:1740-1745.
18. Jhaveri R, et al.: High titer multiple dose therapy with HBIG in newborn infants of HBsAg positive mothers. J Pediatr 1980; 97:305-308.
19. Centers for Disease Control: Hepatitis B virus: A comprehensive strategy for eliminating transmission in the United States through universal childhood vaccination. Recommendations of the Immunization Practices Advisory Committee (ACIP). MMWR 1991; 40(13):1-25.
20. Data on file, Biotest Pharmaceuticals.
21. Scheiermann N, Kuwert EK: Uptake and elimination of hepatitis B immunoglobulins after intramuscular application in man. Develop Biol Standard 1983; 54:347.
22. Centers for Disease Control: General recommendations on immunization. Recommendations of the Advisory Committee on Immunization Practices (ACIP). MMWR 1994; 43:1-38.
23. Ellis EF, Henney CS: Adverse reactions following administration of human gamma globulin. J Allerg 1969; 43:45-54.

Manufactured by: ADMA Biologics, Inc. Boca Raton, FL 33487
U.S. License No. 2019
April 2025